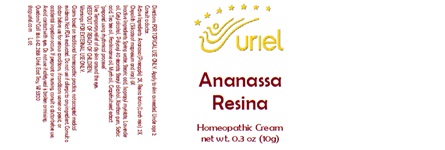 DRUG LABEL: Ananassa Resina
NDC: 48951-1331 | Form: CREAM
Manufacturer: Uriel Pharmacy Inc.
Category: homeopathic | Type: HUMAN OTC DRUG LABEL
Date: 20240513

ACTIVE INGREDIENTS: SILICON DIOXIDE 6 [hp_X]/1 g; PINEAPPLE 2 [hp_X]/1 g; LARIX DECIDUA RESIN 2 [hp_X]/1 g
INACTIVE INGREDIENTS: WATER; STEARIC ACID; ISOPROPYL MYRISTATE; LAVENDER OIL; CETYL ALCOHOL; POLYOXYL 40 STEARATE; STEARYL ALCOHOL; XANTHAN GUM; SORBIC ACID; FRANKINCENSE OIL; MYRRH OIL; CITRUS PARADISI SEED; TEA TREE OIL

Ananassa Resina

INDICATIONS AND USAGE

Directions: FOR TOPICAL USE ONLY.

DOSAGE AND ADMINISTRATION

Apply to skin as needed. Under age 2: Consult a doctor.

ACTIVE INGREDIENT

Active Ingredients: Ananassa (Pineapple) 2X, Resina laricis (Larch resin) 2X, Chrysolith (Silicate of magnesium and iron) 6X

INACTIVE INGREDIENT

Inactive Ingredients: Spring water, Stearic acid, Isopropyl myristate, Lavender oil, Cetyl alcohol, Polyoxyl 40 stearate, Stearyl alcohol, Xanthan gum, Sorbic acid, Tea tree oil, Frankincense oil, Myrrh oil, Grapefruit seed extract

"prepared using rhythmical processes"

PURPOSE

Use: Temporary relief of dry skin around the eyes.

KEEP OUT OF REACH OF CHILDREN.

Warnings: FOR EXTERNAL USE ONLY.
Claims based on traditional homeopathic practice, not accepted medical evidence. Not FDA evaluated. Do not use if allergic to any ingredient. Consult a doctor before use for serious conditions, if conditions worsen or persist, or accidental ingestion occurs. If pregnant or nursing, consult a doctor before use. Avoid contact with eyes. Do not use if safety seal is broken or missing.

Questions? Call 866.642.2858
Uriel, East Troy, WI 53120
shopuriel.com Lot: